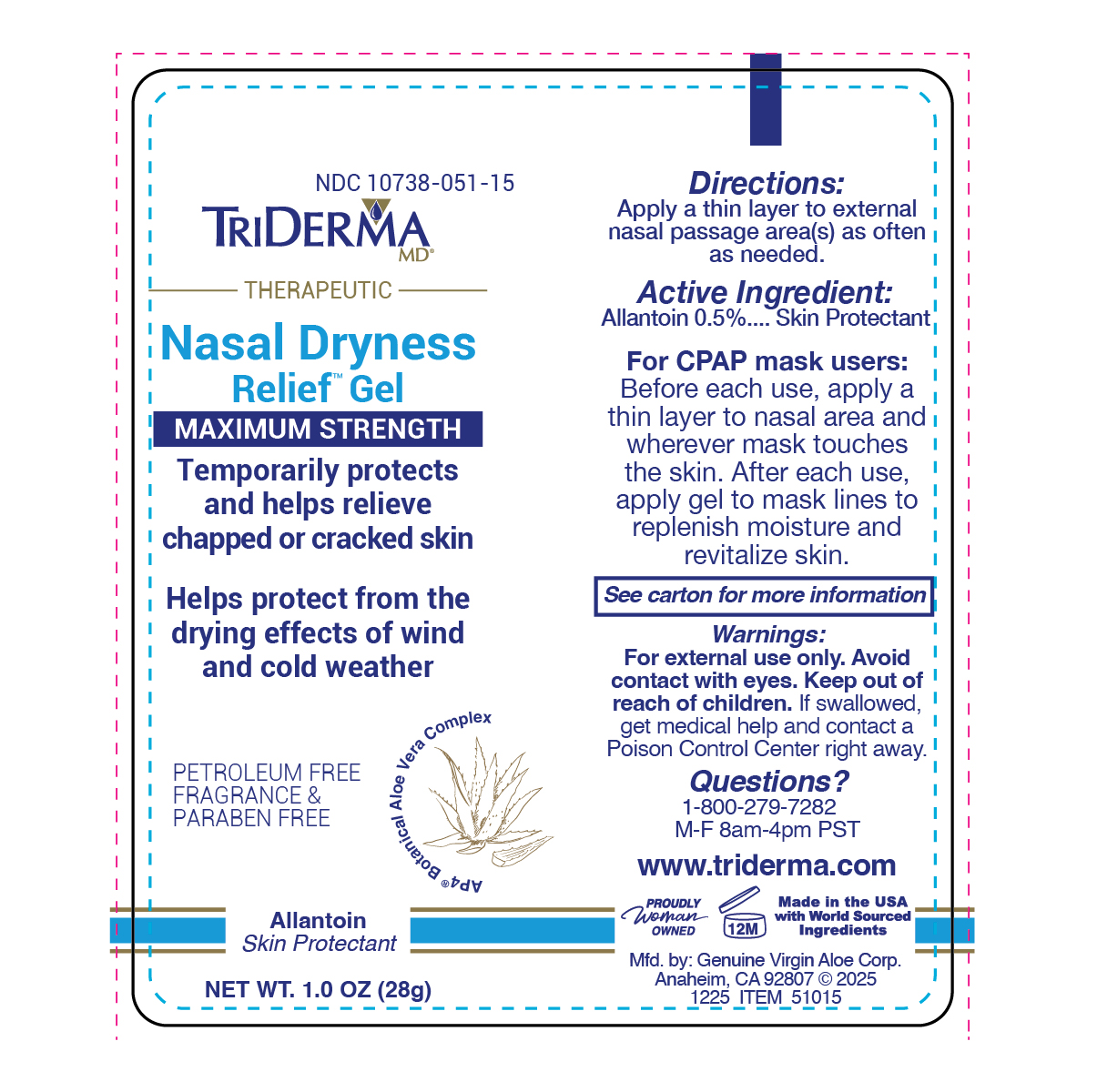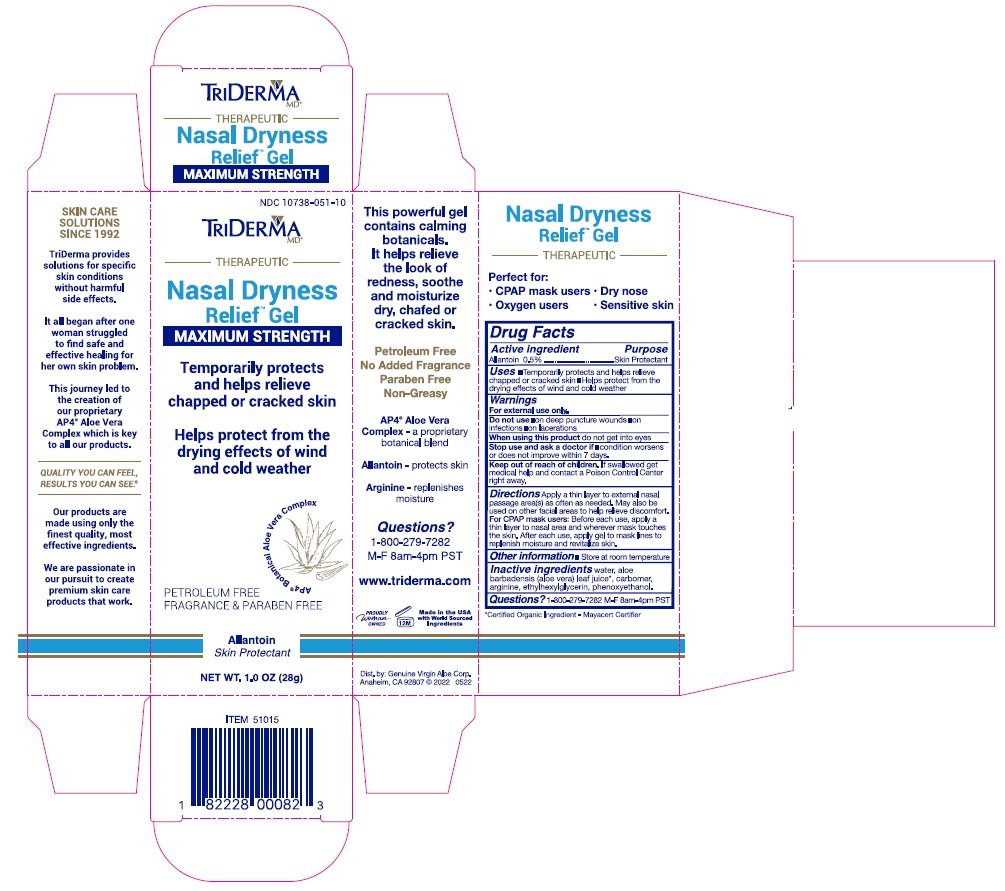 DRUG LABEL: Nasal Dryness Relief Gel
NDC: 10738-051 | Form: GEL
Manufacturer: Genuine Virgin Aloe Corporation
Category: otc | Type: HUMAN OTC DRUG LABEL
Date: 20260127

ACTIVE INGREDIENTS: ALLANTOIN 0.5 g/100 g
INACTIVE INGREDIENTS: ALOE VERA LEAF; ARGININE; ETHYLHEXYLGLYCERIN; PHENOXYETHANOL; CARBOMER 934; WATER

TriDerma Nasal Dryness Relief Gel

Active ingredient

Allantoin 0.5%

Purpose

Skin Protectant

Uses

- Temporarily protects and helps relieve chapped or cracked skin
- Helps protect from the drying effects of wind and cold weather

Warnings

For external use only.

Don not use

- on deep puncture wounds
- on infection
- on lacerations

When using this product

do not get into eyes

Stop use and ask a doctor if

condition worsens or does not improve within 7 days.

Keep out of reach of children.

If swallowed get medical help and contact a Poison Control Center right away,.

Directions

Apply a thin layer to external nasal passages area(s) as often as needed. May also be used on other facial areas to help relieve disconfort.

For CPAP mask users: Before each use, apply a thin layer to nasal area and wherever mask touches the skin. After each use, apply gel to mask lines to replenish moisture and revitalize skin.

Other information

- Store at room temperature

Questions?

1-800-279-7282 M-F 8am-4pm PST

Inactive Ingredients

water, aloe barbadensis (aloe vera) leaf juice*, carbomer, arginine, ethylhexylglycerin, phenoxyethanol.

*Certified Organic Ingredient - Mayacert Certifier

Indications & Usage Section

Temporarily protects and helps relieve chapped or cracked skin * Helps protect from the drying effects of wind and cold weather

Labels

Nasal Dryness Relief_1oz_label